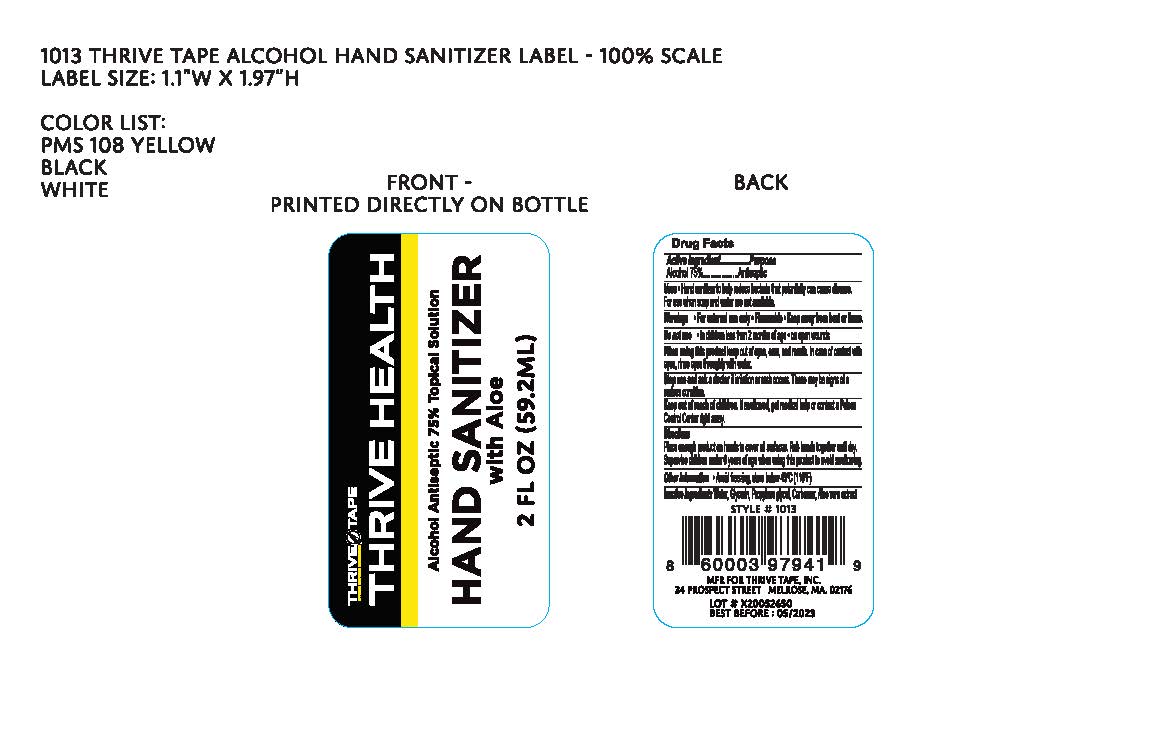 DRUG LABEL: Thrive Health Hand Sanitizer
NDC: 75448-322 | Form: GEL
Manufacturer: Sanrace Biotechnology Co., Ltd.
Category: otc | Type: HUMAN OTC DRUG LABEL
Date: 20200520

ACTIVE INGREDIENTS: ALCOHOL 75 mL/100 mL
INACTIVE INGREDIENTS: WATER; GLYCERIN; PROPYLENE GLYCOL; CARBOMER HOMOPOLYMER, UNSPECIFIED TYPE; ALOE VERA LEAF

Thrive Health Hand Sanitizer with Aloe

Active Ingredient

Ethyl Alcohol 75% v/v

Purpose

Antiseptic

Use[s]

Hand sanitizer to help reduce bacteria that potentially can cause disease.

For use when soap and water are not available.

Warnings

For external use only. Flammable. Keep away from heat or flame.

Do not use

- in children less than 2 months of age
- on open wounds

When using this product keep out of eyes, ears, and mouth. In case of contact with eyes, rinse eyes thoroughly with water.

Stop use and ask a doctor if irritation or rash occurs. These may be signs of a serious condition.

Keep out of reach of children. If swallowed, get medical help or contact a Poison Control Center right away.

Directions

- Place enough product on hands to cover all surfaces. Rub hands together until dry.
- Supervise children under 6 years of age when using this product to avoid swallowing.

Other information

- Avoid freezing, store below 43°C (110°F)

INACTIVE INGREDIENT

Inactive Ingredients: Water, Glycerin, Propylene glycol, Carbomer, Aloe vera extract